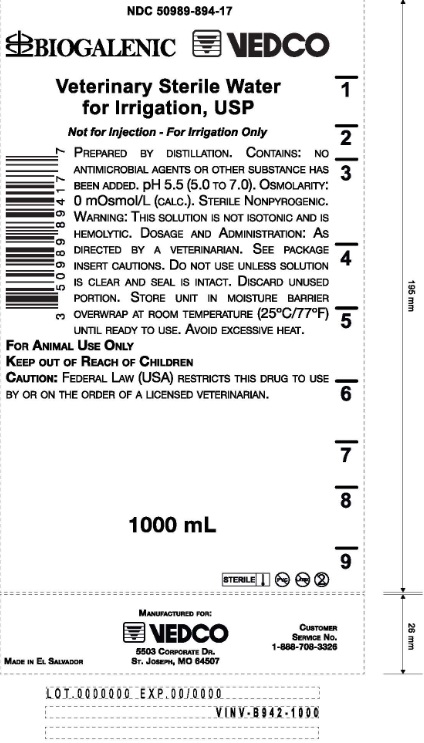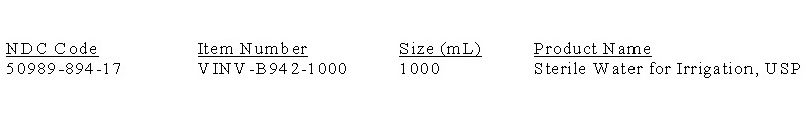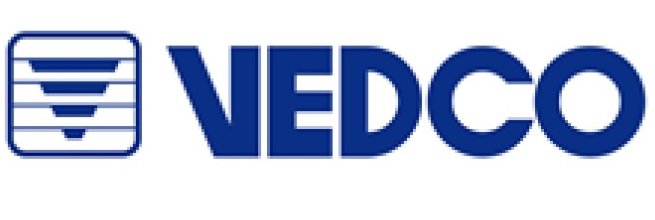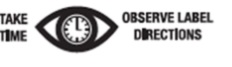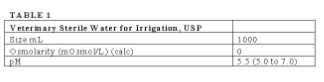 DRUG LABEL: Veterinary Sterile Water for Irrigation
NDC: 50989-894 | Form: IRRIGANT
Manufacturer: Vedco, Inc.
Category: animal | Type: PRESCRIPTION ANIMAL DRUG LABEL
Date: 20170316

ACTIVE INGREDIENTS: WATER 100 g/100 mL

Veterinary Sterile Water For Irrigation, USP

For Animal Use Only

Description

Prepared by distillation. Contains no antimicrobial agents or other substance has been added. Discard unused portion. Sterile, nonpyrogenic. Osmolarity and pH are shown in Table 1:

Contraindications:

None known

Warnings

This solution is not isotonic and is hemolytic.

Dosage and administration:

As directed by a veterinarian.

Cautions

Warm to not more than (50^0C/122^0F) for a maximum of 60 days. Discard unopened bottle after 60 days of warming. Do not use unless solution is clear and seal is intact. Discard unused portion.

How Supplied:

Veterinary Sterile Water for Irrigation, USP in plastic container is available as follows:

Plastic Container:
PVC Free, DEHP Free, Latex Free

Storage

Exposure of pharmaceutical products to heat should be minimized. Avoid excessive heat. it is recommended the product be stored in the moisture overwrap at room temperature (25^0C/77^0F), brief exposure up to (40^0C/104^0F)does not adversely affect the product.

Directions for use of plastic container

To Open

Tear overwrap down side at slit and remove solution container. Some opacity of the plastic due to moisture absorption during the sterilization may be observed. this is normal and does not affect the solution quality or the safety. the opacity will diminish gradually. Check for minute leaks by squeezing inner bag firmly. If leaks are found, discard solution as sterility may be impaired.

Not for injection, for irrigation only.

CAUTION: Federal law restricts this drug to use by or on the order of a licensed veterinarian

Manufacture for:

Vedco, Inc.

5503 Corporate Dr.

St. Joseph, MO 64507 USA

Printed in El Salvador

For a copy of the Safety Data Sheet (MSDS) or to report adverse reaction call Vedco, Inc. customer service at 1(888)708-336

© 2015 Vedco, Inc.

Principal Display Panel

NDC 50989-894-17

BIOGALENIC VEDCO

Veterinary Sterile Water for Irrigation, USP

Not for Injection - For Irrigation Only